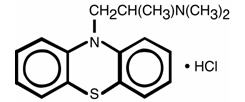 DRUG LABEL: Unknown
Manufacturer: Watson Laboratories, Inc.
Category: prescription | Type: HUMAN PRESCRIPTION DRUG LABELING
Date: 20060405

PROMETHAZINE HCl INJECTION USP
Rx Only

DESCRIPTION

Promethazine HCl Injection USP is a sterile, pyrogen-free solution for deep intramuscular or intravenous administration. Promethazine HCl (10H-phenothiazine-10-ethanamine, N,N,α-trimethyl-, monohydrochloride, (±)-) is a racemic compound and has the following structural formula:

C17H21ClN2S MW = 320.89

Each mL contains: Promethazine HCl 25 mg or 50 mg, Edetate Disodium 0.1 mg, Calcium Chloride 0.04 mg, Sodium Metabisulfite 0.25 mg, with Phenol 5 mg as preservative, in Water for Injection, q.s. Buffered with Glacial Acetic Acid and Sodium Acetate, Trihydrate. The pH range is 4.0 to 5.5. Sealed under Nitrogen.

Promethazine HCl Injection is a clear, colorless solution. The product is light sensitive. It should be inspected before use and discarded if either color or particulate is observed.

CLINICAL PHARMACOLOGY

Promethazine HCl is a phenothiazine derivative which possesses antihistaminic, sedative, antimotion sickness, antiemetic, and anticholinergic effects. Promethazine is a competitive H1 receptor antagonist, but does not block the release of histamine. Structural differences from the neuroleptic phenothiazines results in its relative lack (1/10) of dopamine antagonist properties. In therapeutic doses, promethazine HCl produces no significant effects on the cardiovascular system. Clinical effects are generally apparent within 5 minutes of an intravenous injection and within 20 minutes of an intramuscular injection. Duration of action is four to six hours, although effects may persist up to 12 hours. Promethazine HCl is metabolized in the liver, with the sulfoxides of promethazine and N-desmethylpromethazine being the predominant metabolites appearing in the urine. Following intravenous administration in healthy volunteers, the plasma half-life for promethazine has been reported to range from 9 to 16 hours. The mean plasma half-life for promethazine after intramuscular administration in healthy volunteers has been reported to be 9.8±3.4 hours.

INDICATIONS AND USAGE

Promethazine HCl Injection is indicated for the following conditions:

1. Amelioration of allergic reactions to blood or plasma.
2. In anaphylaxis as an adjunct to epinephrine and other standard measures after the acute symptoms have been controlled.
3. For other uncomplicated allergic conditions of the immediate type when oral therapy is impossible or contraindicated.
4. For sedation and relief of apprehension and to produce light sleep from which the patient can be easily aroused.
5. Active treatment of motion sickness.
6. Prevention and control of nausea and vomiting associated with certain types of anesthesia and surgery.
7. As an adjunct to analgesics for the control of postoperative pain.
8. Preoperative, postoperative, and obstetric (during labor) sedation.
9. Intravenously in special surgical situations, such as repeated bronchoscopy, ophthalmic surgery, and poor-risk patients, with reduced amounts of meperidine or other narcotic analgesic as an adjunct to anesthesia and analgesia.

CONTRAINDICATIONS

Promethazine HCl Injection is contraindicated in comatose states and in patients who have demonstrated an idiosyncrasy or hypersensitivity to promethazine or other phenothiazines.

Under no circumstances should Promethazine HCl Injection be given by intra-arterial injection due to the likelihood of severe arteriospasm and the possibility of resultant gangrene (see “WARNINGS - Inadvertent Intra-arterial Injection”).

Promethazine HCl Injection should not be given by the subcutaneous route; evidence of chemical irritation has been noted, and necrotic lesions have resulted on rare occasions following subcutaneous injection. The preferred parenteral route of administration is by deep intramuscular injection.

WARNINGS

BOXED WARNING

PROMETHAZINE HCl SHOULD NOT BE USED IN PEDIATRIC PATIENTS LESS THAN 2 YEARS OF AGE BECAUSE OF THE POTENTIAL FOR FATAL RESPIRATORY DEPRESSION.

POSTMARKETING CASES OF RESPIRATORY DEPRESSION, INCLUDING FATALITIES, HAVE BEEN REPORTED WITH USE OF PROMETHAZINE HCl IN PEDIATRIC PATIENTS LESS THAN 2 YEARS OF AGE. A WIDE RANGE OF WEIGHT-BASED DOSES OF PROMETHAZINE HCl HAVE RESULTED IN RESPIRATORY DEPRESSION IN THESE PATIENTS.

CAUTION SHOULD BE EXERCISED WHEN ADMINISTERING PROMETHAZINE HCl TO PEDIATRIC PATIENTS 2 YEARS OF AGE AND OLDER. IT IS RECOMMENDED THAT THE LOWEST EFFECTIVE DOSE OF PROMETHAZINE HCl BE USED IN PEDIATRIC PATIENTS 2 YEARS OF AGE AND OLDER AND CONCOMITANT ADMINISTRATION OF OTHER DRUGS WITH RESPIRATORY DEPRESSANT EFFECTS BE AVOIDED.

Sulfite Sensitivity

Promethazine HCl Injection contains sodium metabisulfite, a sulfite that may cause allergic-type reactions, including anaphylactic symptoms and life-threatening or less severe asthma episodes, in certain susceptible people. The overall prevalence of sulfite sensitivity in the general population is unknown and probably low. Sulfite sensitivity is seen more frequently in asthmatic than in nonasthmatic people.

CNS Depression

Promethazine HCl Injection may impair the mental and physical abilities required for the performance of potentially hazardous tasks, such as driving a vehicle or operating machinery. The impairment may be amplified by concomitant use of other central nervous system depressants such as alcohol, sedative-hypnotics (including barbiturates), general anesthetics, narcotics, narcotic analgesics, tranquilizers, etc. (see “PRECAUTIONS - Information for Patients”).

Lower Seizure Threshold

Promethazine HCl Injection may lower seizure threshold and should be used with caution in persons with seizure disorders or in persons who are using concomitant medications, such as narcotics or local anesthetics, which may also affect seizure threshold.

Bone Marrow Depression

Promethazine HCl Injection should be used with caution in patients with bone marrow depression. Leukopenia and agranulocytosis have been reported, usually when promethazine HCl has been used in association with other known marrow-toxic agents.

Use in Pediatric Patients

PROMETHAZINE HCl INJECTION IS CONTRAINDICATED FOR USE IN PEDIATRIC PATIENTS LESS THAN TWO YEARS OF AGE.

CAUTION SHOULD BE EXERCISED WHEN ADMINISTERING PROMETHAZINE HCl INJECTION TO PEDIATRIC PATIENTS 2 YEARS OF AGE AND OLDER BECAUSE OF THE POTENTIAL FOR FATAL RESPIRATORY DEPRESSION. RESPIRATORY DEPRESSION AND APNEA, SOMETIMES ASSOCIATED WITH DEATH, ARE STRONGLY ASSOCIATED WITH PROMETHAZINE PRODUCTS AND NOT FIRMLY WEIGHT-RELATED, WHICH MIGHT OTHERWISE PERMIT SAFE ADMINISTRATION OF INDIVIDUALIZED DOSING. CONCOMITANT ADMINISTRATION OF PROMETHAZINE PRODUCTS WITH OTHER RESPIRATORY DEPRESSANTS HAS AN ASSOCIATION WITH RESPIRATORY DEPRESSION, AND SOMETIMES DEATH, IN PEDIATRIC PATIENTS.

ANTIEMETICS ARE NOT RECOMMENDED FOR TREATMENT OF UNCOMPLICATED VOMITING IN PEDIATRIC PATIENTS, AND THEIR USE SHOULD BE LIMITED TO PROLONGED VOMITING OF KNOWN ETIOLOGY. THE EXTRAPYRAMIDAL SYMPTOMS WHICH CAN OCCUR SECONDARY TO PROMETHAZINE HCl INJECTION ADMINISTRATION MAY BE CONFUSED WITH THE CNS SIGNS OF UNDIAGNOSED PRIMARY DISEASE, e.g., ENCEPHALOPATHY OR REYE'S SYNDROME. THE USE OF PROMETHAZINE HCl INJECTION SHOULD BE AVOIDED IN PEDIATRIC PATIENTS WHOSE SIGNS AND SYMPTOMS MAY SUGGEST REYE'S SYNDROME OR OTHER HEPATIC DISEASES.

Excessively large dosages of antihistamines, including Promethazine HCl Injection, in pediatric patients may cause hallucinations, convulsions, and sudden death. In pediatric patients who are acutely ill associated with dehydration, there is an increased susceptibility to dystonias with the use of Promethazine HCl Injection.

Inadvertent Intra-arterial Injection

Due to the close proximity of arteries and veins in the areas most commonly used for intravenous injection, extreme care should be exercised to avoid perivascular extravasation or inadvertent intra-arterial injection. Reports compatible with inadvertent intra-arterial injection of Promethazine HCl Injection, usually in conjunction with other drugs intended for intravenous use, suggest that pain, severe chemical irritation, severe spasm of distal vessels, and resultant gangrene requiring amputation are likely under such circumstances. Intravenous injection was intended in all the cases reported but perivascular extravasation or arterial placement of the needle is now suspect. There is no proven successful management of this condition after it occurs, although sympathetic block and heparinization are commonly employed during the acute management because of the results of animal experiments with other known arteriolar irritants. Aspiration of dark blood does not preclude intra-arterial needle placement, because blood is discolored upon contact with Promethazine HCl Injection. Use of syringes with rigid plungers or of small bore needles might obscure typical arterial backflow if this is relied upon alone.

When used intravenously, Promethazine HCl Injection should be given in a concentration no greater than 25 mg per mL and at a rate not to exceed 25 mg per minute. When administering any irritant drug intravenously, it is usually preferable to inject it through the tubing of an intravenous infusion set that is known to be functioning satisfactorily. In the event that a patient complains of pain during intended intravenous injection of Promethazine HCl Injection, the injection should be stopped immediately to provide for evaluation of possible arterial placement or perivascular extravasation.

Visual Inspection

This product is light sensitive and should be inspected before use and discarded if either color or particulate is observed.

Other Considerations

Sedative drugs or CNS depressants should be avoided in patients with a history of sleep apnea. Administration of promethazine has been associated with reported cholestatic jaundice.

PRECAUTIONS

General

Drugs having anticholinergic properties should be used with caution in patients with narrow-angle glaucoma, prostatic hypertrophy, stenosing peptic ulcer, pyloroduodenal obstruction, and bladder-neck obstruction.

Promethazine HCl Injection should be used cautiously in persons with cardiovascular disease or impairment of liver function.

Information for Patients

Promethazine HCl Injection may cause marked drowsiness or impair the mental or physical abilities required for the performance of potentially hazardous tasks, such as driving a vehicle or operating machinery. The use of alcohol, sedative-hypnotics (including barbiturates), general anesthetics, narcotics, narcotic analgesics, tranquilizers, etc. with Promethazine HCl Injection may enhance impairment. Pediatric patients should be supervised to avoid potential harm in bike riding or in other hazardous activities.

Patients should be advised to report any involuntary muscle movements.

Persistent or worsening pain or burning at the injection site should be reported immediately.

Avoid prolonged exposure to the sun.

Drug Interactions

CNS Depressants -
Promethazine HCl Injection may increase, prolong, or intensify the sedative action of central nervous system depressants, such as alcohol, sedative-hypnotics (including barbiturates), general anesthetics, narcotics, narcotic analgesics, tranquilizers, etc. When given concomitantly with Promethazine HCl Injection, the dose of barbiturates should be reduced by at least one-half, and the dose of narcotics should be reduced by one-quarter to one-half. Dosage must be individualized. Excessive amounts of Promethazine HCl Injection relative to a narcotic may lead to restlessness and motor hyperactivity in the patient with pain; these symptoms usually disappear with adequate control of the pain.

Epinephrine -
Although reversal of the vasopressor effect of epinephrine has not been reported with Promethazine HCl Injection, it is recommended that epinephrine NOT be used in the case of Promethazine HCl Injection overdose.

Anticholinergics -
Concomitant use of other agents with anticholinergic properties should be undertaken with caution.

Monoamine Oxidase Inhibitors (MAOI) -
Drug interactions, including an increased incidence of extrapyramidal effects, have been reported when some MAOI and phenothiazines are used concomitantly. Although such a reaction has not been reported with Promethazine HCl Injection, the possibility should be considered.

Laboratory Tests Interactions

The following laboratory tests may be affected in patients who are receiving therapy with Promethazine HCl Injection:

Pregnancy Tests -
Diagnostic pregnancy tests based on immunological reactions between HCG and anti-HCG may result in false-negative or false-positive interpretations.

Glucose Tolerance Test -
An increase in glucose tolerance has been reported in patients receiving promethazine HCl.

Carcinogenesis, Mutagenesis, and Impairment of Fertility

Long term animal studies have not been performed to assess the carcinogenic potential of Promethazine HCl Injection, nor are there other animal or human data concerning carcinogenicity, mutagenicity, or impairment of fertility. Promethazine HCl Injection was nonmutagenic in the Ames Salmonella test system.

Pregnancy

Teratogenic Effects – Pregnancy Category C:

Teratogenic effects have not been demonstrated in rat feeding studies at doses of 6.25 and 12.5 mg/kg (approximately 2.1 and 4.2 times the maximum recommended human daily dose) of Promethazine HCl Injection. Daily doses of 25 mg/kg intraperitoneally have been found to produce fetal mortality in rats.

There are no adequate and well-controlled studies of Promethazine HCl Injection in pregnant women. Because animal reproduction studies are not always predictive of human response, Promethazine HCl Injection should be used during pregnancy only if the potential benefit justifies the potential risk to the fetus.

Adequate studies to determine the action of the drug on parturition, lactation and development of the animal neonate have not been conducted.

Nonteratogenic Effects

Promethazine HCl Injection received within two weeks of delivery may inhibit platelet aggregation in the newborn.

Labor and Delivery

Promethazine HCl Injection may be used alone or as an adjunct to narcotic analgesics during labor (see “DOSAGE AND ADMINISTRATION”). Limited data suggest that use of Promethazine HCl Injection during labor and delivery does not have an appreciable effect on the duration of labor or delivery and does not increase the risk of need for intervention in the newborn. The effect on later growth and development of the newborn is unknown. (See also “Pregnancy: Nonteratogenic Effects.”)

Nursing Mothers

It is not known whether Promethazine HCl Injection is excreted in human milk. Because many drugs are excreted in human milk, caution should be exercised when Promethazine HCl Injection is administered to a nursing woman.

Pediatric Use

Safety and effectiveness in pediatric patients under 2 years of age have not been established.

Promethazine HCl Injection should be used with caution in pediatric patients 2 years of age and older (see “WARNINGS - Use in Pediatric Patients”).

Use in Geriatric Patients (Approximately 60 Years or Older)

Since therapeutic requirements for sedative drugs tend to be less in geriatric patients, the dosage should be reduced for these patients.

ADVERSE REACTIONS

CNS Effects:

Drowsiness is the most prominent CNS effect of this drug. Extrapyramidal reactions may occur with high doses; this is almost always responsive to a reduction in dosage. Other reported reactions include dizziness, lassitude, tinnitus, incoordination, fatigue, blurred vision, euphoria, diplopia, nervousness, insomnia, tremors, convulsive seizures, oculogyric crises, excitation, catatonic-like states, hysteria, and hallucinations.

Cardiovascular Effects:

Tachycardia, bradycardia, faintness, dizziness, and increases and decreases in blood pressure have been reported following the use of Promethazine HCl Injection. Venous thrombosis at the injection site has been reported. INTRA-ARTERIAL INJECTION MAY RESULT IN GANGRENE OF THE AFFECTED EXTREMITY (see “WARNINGS - Inadvertent Intra-arterial Injection”).

Gastrointestinal Effects:

Nausea and vomiting have been reported, usually in association with surgical procedures and combination drug therapy.

Allergic Reactions:

These include urticaria, dermatitis, asthma, and photosensitivity. Angioneurotic edema has been reported.

Other Reported Reactions:

Leukopenia and agranulocytosis, usually when promethazine HCl has been used in association with other known marrow-toxic agents, have been reported. Thrombocytopenic purpura and jaundice of the obstructive type have been associated with the use of promethazine HCl. The jaundice is usually reversible on discontinuation of the drug. Subcutaneous injection has resulted in tissue necrosis. Nasal stuffiness may occur. Dry mouth has been reported.

Paradoxical Reactions (Overdosage):

Hyperexcitability and abnormal movements, which have been reported in pediatric patients following a single administration of Promethazine HCl Injection, may be manifestations of relative overdosage, in which case, consideration should be given to the discontinuation of Promethazine HCl Injection and to the use of other drugs. Respiratory depression, nightmares, delirium, and agitated behavior have also been reported in some of these patients.

OVERDOSAGE

Signs and symptoms of overdosage range from mild depression of the central nervous system and cardiovascular system to profound hypotension, respiratory depression, and unconsciousness.

Stimulation may be evident, especially in pediatric patients and geriatric patients. Convulsions may rarely occur. A paradoxical reaction has been reported in pediatric patients receiving single doses of 75 mg to 125 mg orally, characterized by hyperexcitability and nightmares.

Atropine-like signs and symptoms - dry mouth; fixed, dilated pupils; flushing; etc., as well as gastrointestinal symptoms, may occur.

Treatment:

Treatment of overdosage is essentially symptomatic and supportive. Only in cases of extreme overdosage or individual sensitivity do vital signs, including respiration, pulse, blood pressure, temperature, and EKG, need to be monitored. Attention should be given to the reestablishment of adequate respiratory exchange through provision of a patent airway and institution of assisted or controlled ventilation. Diazepam may be used to control convulsions. Acidosis and electrolyte losses should be corrected. Note that any depressant effects of Promethazine HCl Injection are not reversed by naloxone.

Avoid analeptics, which may cause convulsions. The treatment of choice for resulting hypotension is administration of intravenous fluids, accompanied by repositioning if indicated. In the event that vasopressors are considered for the management of severe hypotension which does not respond to intravenous fluids and repositioning, the administration of levarterenol or phenylephrine should be considered. EPINEPHRINE SHOULD NOT BE USED, since its use in a patient with partial adrenergic blockade may further lower the blood pressure. Extrapyramidal reactions may be treated with anticholinergic antiparkinson agents, diphenhydramine, or barbiturates. Oxygen may also be administered. Limited experience with dialysis indicates that it is not helpful.

DOSAGE AND ADMINISTRATION

Parenteral drug products should be inspected visually for particulate matter and discoloration prior to administration, whenever solution and container permit.

Do not use Promethazine HCl Injection if solution has developed color or contains precipitate.

To avoid the possibility of physical and/or chemical incompatibility, consult specialized literature before diluting with any injectable solution or combining with any other medication. Do not use if there is a precipitate or any sign of incompatibility.

Important Notes on Administration: The preferred parenteral route of administration for Promethazine HCl Injection is by deep intramuscular injection. The proper intravenous administration of this product is well-tolerated, but use of this route is not without some hazard. Not for subcutaneous administration.

INADVERTENT INTRA-ARTERIAL INJECTION CAN RESULT IN GANGRENE OF THE AFFECTED EXTREMITY (see “WARNINGS - Inadvertent Intra-arterial Injection”). SUBCUTANEOUS INJECTION IS CONTRAINDICATED, AS IT MAY RESULT IN TISSUE NECROSIS (see “CONTRAINDICATIONS”).

Injection into or near a nerve may result in permanent tissue damage.

When used intravenously, Promethazine HCl Injection should be given in a concentration no greater than 25 mg/mL at a rate not to exceed 25 mg per minute; it is preferable to inject through the tubing of an intravenous infusion set that is known to be functioning satisfactorily.

Allergic Conditions:

The average adult dose is 25 mg. This dose may be repeated within two hours if necessary, but continued therapy, if indicated, should be via the oral route as soon as existing circumstances permit. After initiation of treatment, dosage should be adjusted to the smallest amount adequate to relieve symptoms. The average adult dose for amelioration of allergic reactions to blood or plasma is 25 mg.

Sedation:

In hospitalized adult patients, nighttime sedation may be achieved by a dose of 25 to 50 mg of Promethazine HCl Injection.

Nausea and Vomiting:

For control of nausea and vomiting, the usual adult dose is 12.5 to 25 mg, not to be repeated more frequently than every four hours. When used for control of postoperative nausea and vomiting, the medication may be administered either intramuscularly or intravenously and dosage of analgesics and barbiturates reduced accordingly.

Preoperative and Postoperative Use:

As an adjunct to preoperative or postoperative medication, 25 to 50 mg of Promethazine HCl Injection in adults may be combined with appropriately reduced doses of analgesics and atropine-like drugs as desired. Dosage of concomitant analgesic or hypnotic medication should be reduced accordingly.

Obstetrics:

Promethazine HCl Injection in doses of 50 mg will provide sedation and relieve apprehension in the early stages of labor. When labor is definitely established, 25 to 75 mg (average dose, 50 mg) Promethazine HCl Injection may be given intramuscularly or intravenously with an appropriately reduced dose of any desired narcotic. If necessary, Promethazine HCl Injection with a reduced dose of analgesic may be repeated once or twice at four-hour intervals in the course of a normal labor. A maximum total dose of 100 mg of Promethazine HCl Injection may be administered during a 24-hour period to patients in labor.

Pediatric Patients:

Promethazine HCl Injection is contraindicated for children under 2 years of age (see “WARNINGS - Use in Pediatric Patients”).

In pediatric patients 2 years of age and older, the dosage should not exceed half that of the suggested adult dose. As an adjunct to premedication, the suggested dose is 0.5 mg per lb. of body weight in combination with an appropriately reduced dose of narcotic or barbiturate and the appropriate dose of an atropine-like drug. Antiemetics should not be used in vomiting of unknown etiology in pediatric patients (see “WARNINGS - Use in Pediatric Patients”).

HOW SUPPLIED

Promethazine HCl Injection USP is available as follows:
25 mg/mL, 1 mL ampules, cartons of 25
50 mg/mL, 1 mL ampules, cartons of 25

Store at controlled room temperature 15º-30ºC (59º - 86ºF).

Protect from light. Keep covered in carton until time of use.

Do not use if solution has developed color or contains a precipitate.

Literature revised: June 2004

Product Nos.: 1107-81, 0259-81

Watson Laboratories, Inc.
Corona, CA 92880 USA

695302590591*B1